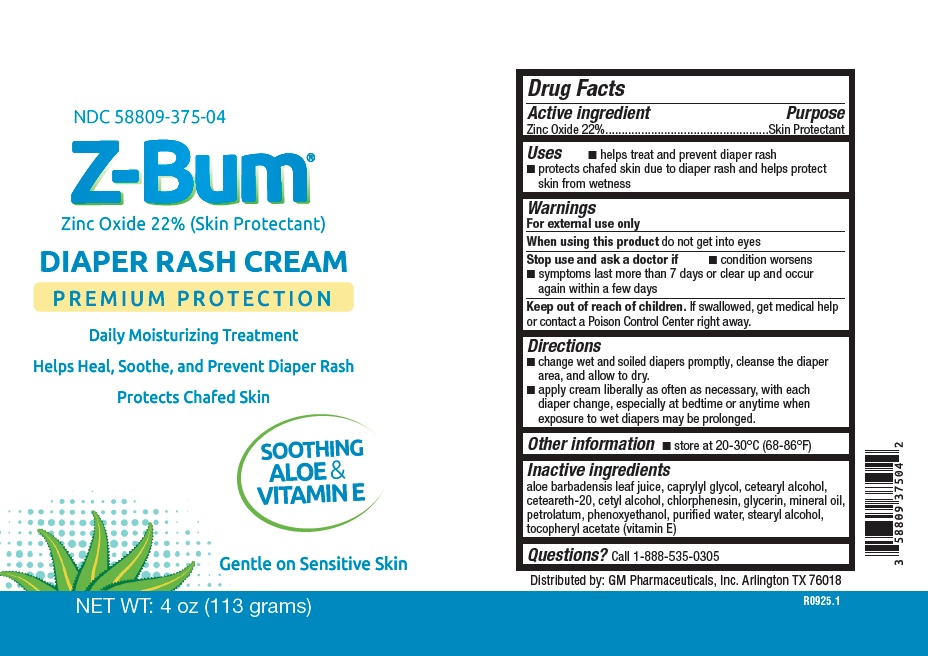 DRUG LABEL: Z-Bum
NDC: 58809-375 | Form: CREAM
Manufacturer: GM Pharmaceuticals, Inc
Category: otc | Type: HUMAN OTC DRUG LABEL
Date: 20260108

ACTIVE INGREDIENTS: ZINC OXIDE 22 g/100 g
INACTIVE INGREDIENTS: CETYL ALCOHOL; CAPRYLYL GLYCOL; LIGHT MINERAL OIL; ALOE VERA LEAF; GLYCERIN; CHLORPHENESIN; WATER; STEARYL ALCOHOL; ALPHA-TOCOPHEROL; PETROLATUM; PHENOXYETHANOL; POLYOXYL 20 CETOSTEARYL ETHER

Z-Bum

Z-Bum

NDC 58809-375-04

4 oz. (113 grams)

Active ingredient

Zinc Oxide 22%

Purpose

Skin Protectant

Uses

■ helps treat and prevent diaper rash

■ protects chafed skin due to diaper rash and helps protect skin from wetness

Warnings

For external use only

When using this product

do not get into eyes.

Stop use and ask a doctor if

■ condition worsens

■ symptoms last more than 7 days or clear up and occur again within a few days

Keep out of reach of children.

If swallowed, get medical help or contact a Poison Control Center right away.

Directions

■ change wet and soiled diapers promptly, cleanse the diaper area, and allow to dry.

■ apply cream liberally as often as necessary, with each diaper change, especially at

bedtime or anytime when exposure to wet diapers may be prolonged.

Other information

■ store at 20-30°C (68-86°F)

Inactive ingredients

aloe barbadensis leaf juice, caprylyl glycol, ceteareth- 20, cetyl alcohol, chlorphenesin, glycerine, mineral oil, petrolatum, phenoxyethanol, purified water, stearyl alcohol, tocopheryl acetate (vitamin E)

Questions or comments?

Call 1-888-535-0305

Distributed by: GM Pharmaceuticals, Inc. Arlington, TX 76018

PRINCIPAL DISPLAY PANEL

NDC 58809-375-04
Z-BUM

Zinc Oxide 22% (Skin Protectant)

Diaper Rash Cream

Premium Protection

Helps heal, soothe, and prevent diaper rash

Protects chafed skin

SOOTHING ALOE & VITAMIN E

Gentle on sensitive skin

NET WT 4 oz (113 grams)